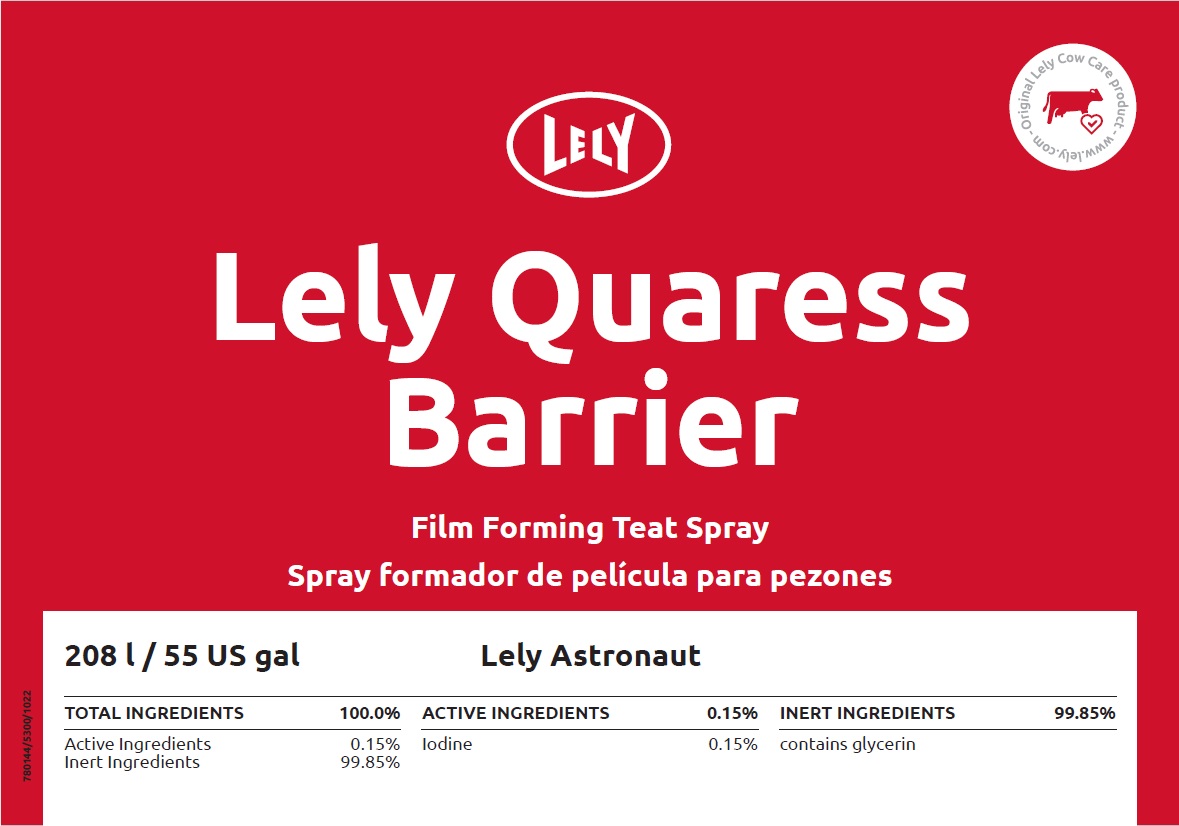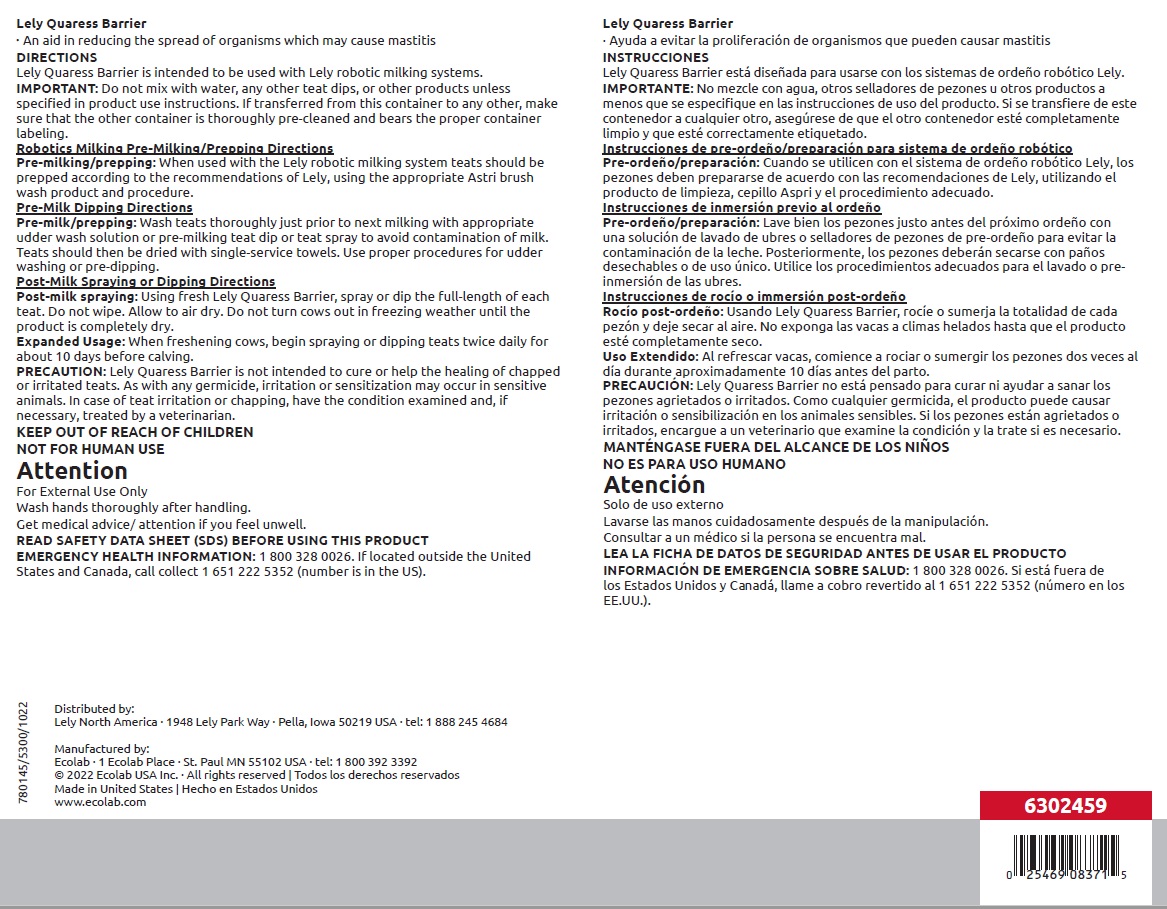 DRUG LABEL: Lely Quaress Barrier
NDC: 86190-001 | Form: SOLUTION
Manufacturer: Lely North America, Inc.
Category: animal | Type: OTC ANIMAL DRUG LABEL
Date: 20240710

ACTIVE INGREDIENTS: IODINE 1.5 mg/1 mL
INACTIVE INGREDIENTS: WATER

KEEP OUT OF REACH OF CHILDREN
NOT FOR HUMAN USE
Attention
For External Use Only
Wash hands thoroughly after handling.
Get medical advice/ attention if you feel unwell.

DIRECTIONS

Lely Quaress Barrier is intended to be used with Lely robotic milking systems. IMPORTANT: Do not mix with water, any other teat dips, or other products unless specified in product use instructions. If transferred from this container to any other, make sure that the other container is thoroughly pre-cleaned and bears the proper container labeling.

Robotics Milking Pre-Milking/Prepping Directions

Pre-milking/prepping: When used with the Lely robotic milking system teats should be prepped according to the recommendations of Lely, using the appropriate Astri brush wash product and procedure.

Pre-Milk Dipping Directions

Pre-milk/prepping: Wash teats thoroughly just prior to next milking with appropriate udder wash solution or pre-milking teat dip or teat spray to avoid contamination of milk. Teats should then be dried with single-service towels. Use proper procedures for udder washing or pre-dipping.

Post-Milk Spraying or Dipping Directions

Post-milk spraying: Using fresh Lely Quaress Barrier, spray or dip the full-length of each teat. Do not wipe. Allow to air dry. Do not turn cows out in freezing weather until the product is completely dry.

Expanded Usage: When freshening cows, begin spraying or dipping teats twice daily for about 10 days before calving.

PRECAUTION: Lely Quaress Barrier is not intended to cure or help the healing of chapped or irritated teats. As with any germicide, irritation or sensitization may occur in sensitive animals. In case of teat irritation or chapping, have the condition examined and, if necessary, treated by a veterinarian.

OTHER SAFETY INFORMATION

READ SAFETY DATA SHEET (SDS) BEFORE USING THIS PRODUCT
EMERGENCY HEALTH INFORMATION: 1 800 328 0026. If located outside the
United States and Canada, call collect 1 651 222 5352 (number is in the US).

Principal display panel and representative label

LELY

Lely Quaress

Barrier

Film Foaming Teat Spray

208 l / 55 US gal Lely Astronaut

TOTAL INGREDIENTS | 100.0% | ACTIVE INGREDIENTS | 0.15% | INERT INGREDIENTS | 99.85%
Active Ingredients | 0.15% | Iodine | 0.15% | contains glycerin
Inert Ingredients | 99.85%

Distributed by:

Lely North America · 1948 Lely Park Way · Pella, Iowa 50219 USA · tel: 1 888 245 4684

Manufactured by:

Ecolab · 1 Ecolab Place · St. Paul MN 55102 USA · tel: 1 800 392 3392

© 2022 Ecolab USA Inc. · All rights reserved

Made in United States